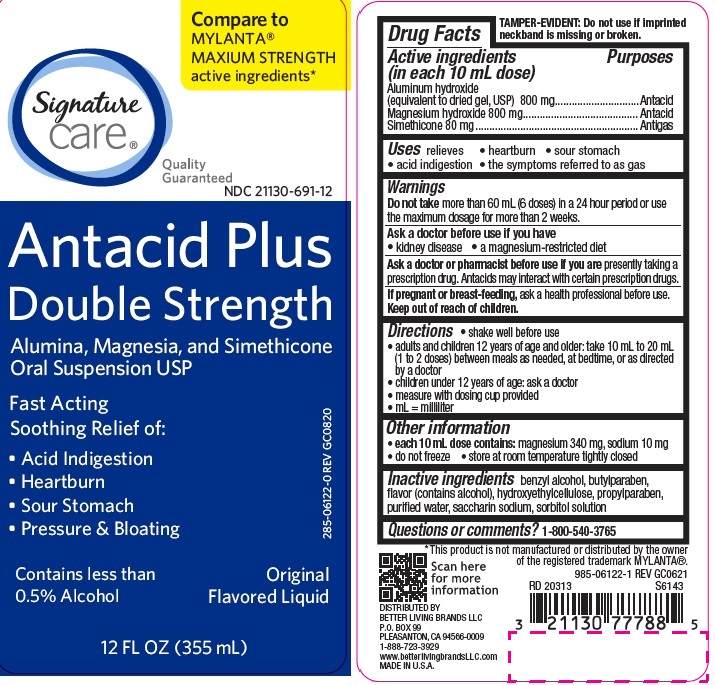 DRUG LABEL: ANTACID PLUS
NDC: 21130-691 | Form: LIQUID
Manufacturer: BETTER LIVING BRANDS LLC
Category: otc | Type: HUMAN OTC DRUG LABEL
Date: 20231107

ACTIVE INGREDIENTS: ALUMINUM HYDROXIDE 800 mg/10 mL; MAGNESIUM HYDROXIDE 800 mg/10 mL; DIMETHICONE 80 mg/10 mL
INACTIVE INGREDIENTS: BENZYL ALCOHOL; BUTYLPARABEN; CARBOXYMETHYLCELLULOSE SODIUM; HYPROMELLOSES; CELLULOSE, MICROCRYSTALLINE; PROPYLPARABEN; WATER; SACCHARIN SODIUM; SORBITOL SOLUTION

sc myl max

Active ingredients (in each 10 mL dose)

Aluminum hydroxide 800 mg (equivalent to dried gel, USP)

Magnesium hydroxide 800 mg

Simethicone 80mg

Purposes

Antacid

Antigas

Uses

relieves

- heartburn
- sour stomach
- acid indigestion
- the symptoms referred to as gas

Warnings

Do not take more than 60 mL (6 doses) in a 24 hour period or use
the maximum dosage for more than 2 weeks.

Ask a doctor before use if you have

• kidney disease

• a magnesium-restricted diet

Ask a doctor or pharmacist before use if you are taking a prescription drug.

Antacids may interact with certain prescription drugs.

If pregnant or breast-feeding, ask a health professional before use.

Keep out of the reach of children.

Directions

- shake well before use
- adults and children 12 years and over: 10 mL-20 mL (1-2 doses) between meals, at bedtime, or as directed by a doctor
- children under 12 years of age: ask a doctor
- measure with dosing cup provided
- mL = milliliter

Other information

- each 10 mL dose contains: magnesium 340 mg; sodium 10 mg
- do not freeze
- store at room temperature tightly closed

Inactive ingredients

benzyl alcohol, butylparaben, carboxymethylcellulose sodium, flavor (contains alcohol), hypromellose, microcrystalline cellulose, propylparaben, purified water, saccharin sodium, sorbitol solution

Questions or comments?

1-800-540-3765